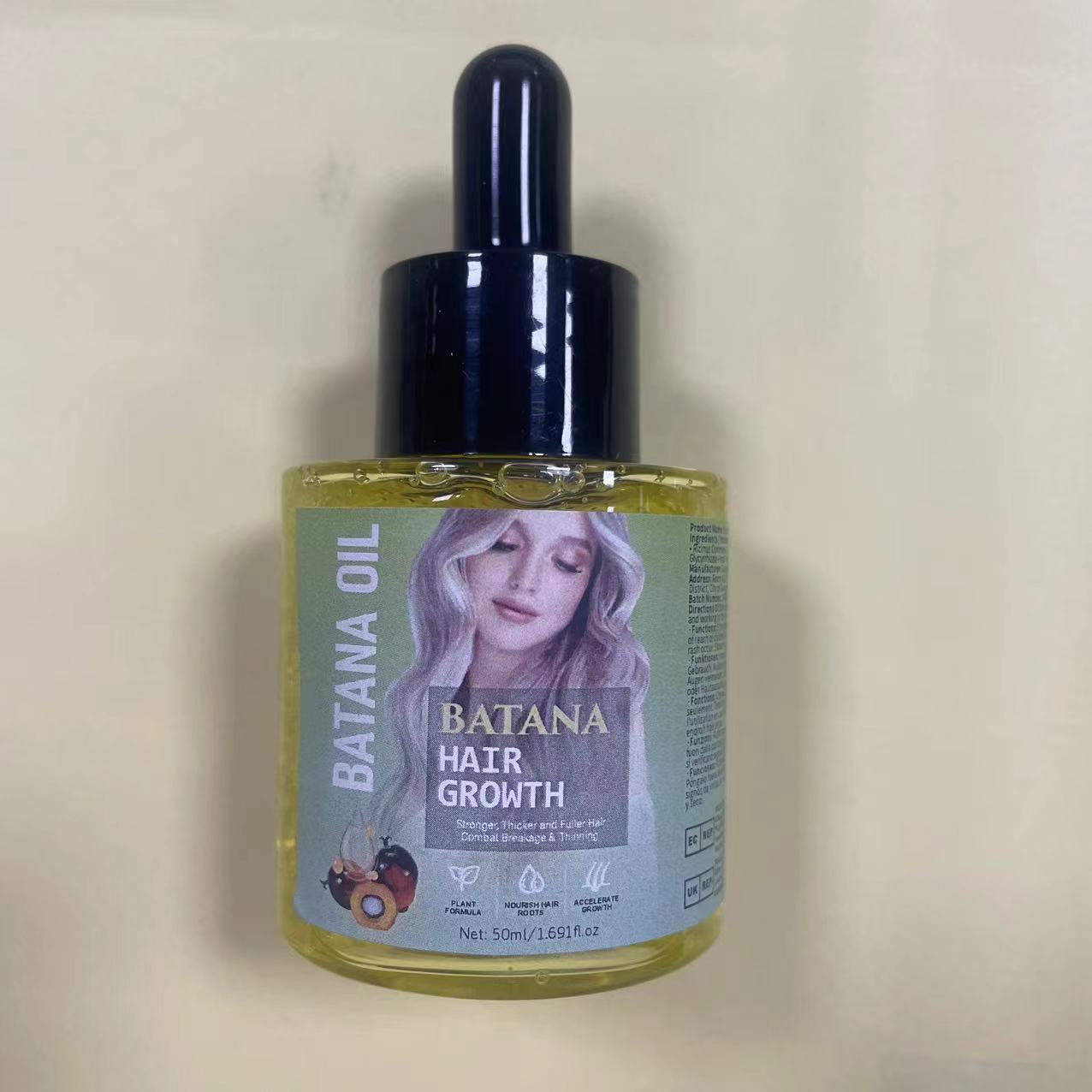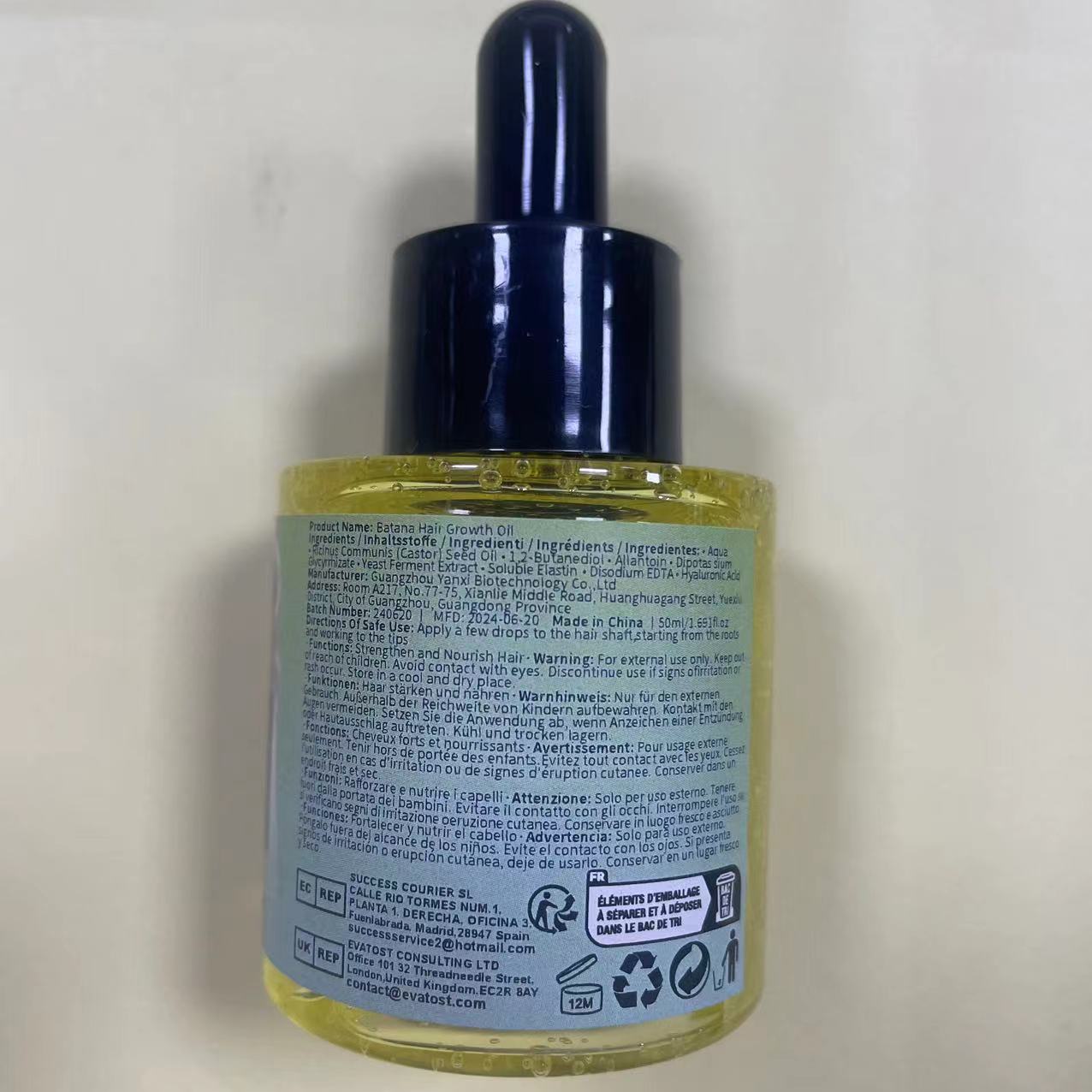 DRUG LABEL: Batana Hair Growth Oil
NDC: 84025-078 | Form: CREAM
Manufacturer: Guangzhou Yanxi Biotechnology Co., Ltd
Category: otc | Type: HUMAN OTC DRUG LABEL
Date: 20240720

ACTIVE INGREDIENTS: ALLANTOIN 3 mg/100 mL; HYALURONIC ACID 5 mg/100 mL
INACTIVE INGREDIENTS: WATER

DOSAGE AND ADMINISTRATION

USE AS A NORMAL HAR CREAM

WARNINGS

Keep out of children

INACTIVE INGREDIENT

Aqua

INDICATIONS AND USAGE

The hair is coarse and falls out badly

Keep out of children

PURPOSE

Improve hair quality and promote hair growth